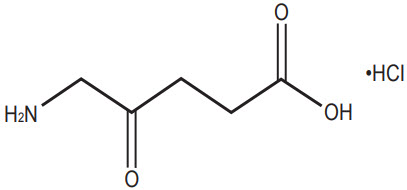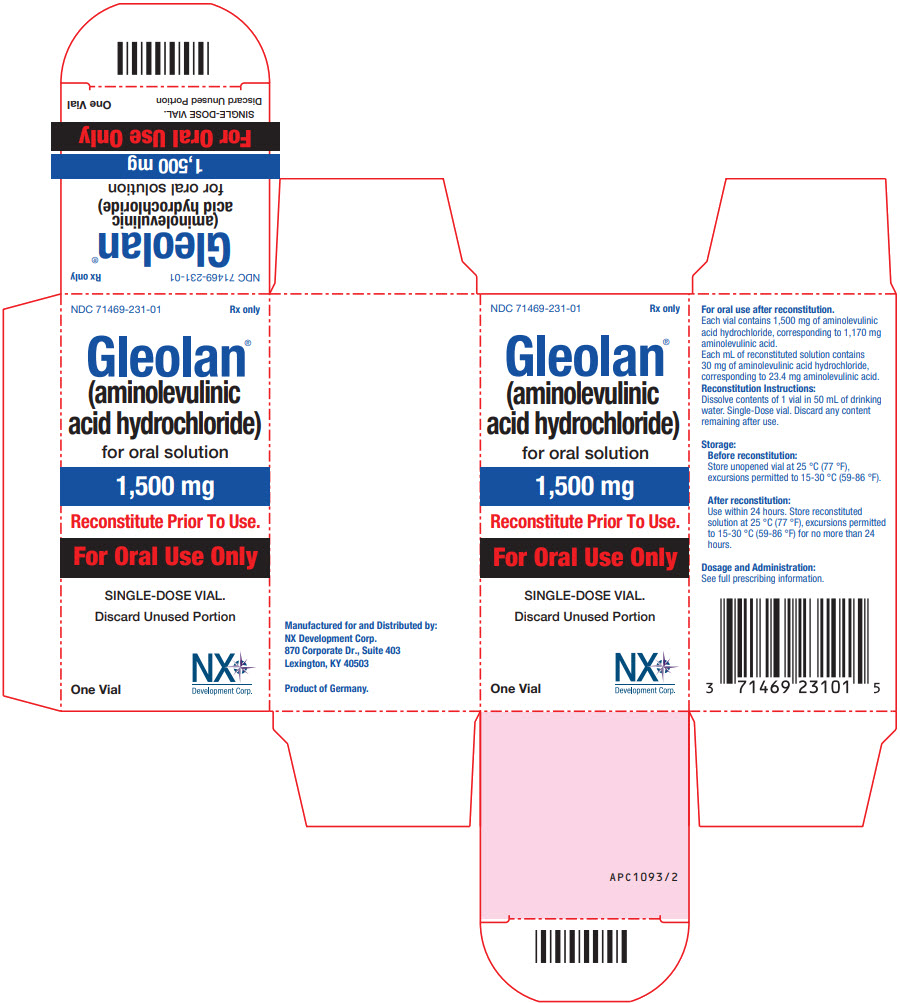 DRUG LABEL: GLEOLAN
NDC: 71469-231 | Form: POWDER, FOR SOLUTION
Manufacturer: NX DEVELOPMENT CORP
Category: prescription | Type: HUMAN PRESCRIPTION DRUG LABEL
Date: 20260129

ACTIVE INGREDIENTS: AMINOLEVULINIC ACID HYDROCHLORIDE 1500 mg/1 1

HIGHLIGHTS OF PRESCRIBING INFORMATION

These highlights do not include all the information needed to use GLEOLAN safely and effectively. See full prescribing information for GLEOLAN.
GLEOLAN® (aminolevulinic acid hydrochloride) for oral solution
Initial U.S. Approval: [1999]

1 INDICATIONS AND USAGE

Gleolan is an optical imaging agent indicated in patients with glioma (suspected World Health Organization Grades III or IV on preoperative imaging) as an adjunct for the visualization of malignant tissue during surgery. (1)

2 DOSAGE AND ADMINISTRATION

- For oral use only (2.1)
- Recommended reconstituted oral dose of Gleolan is 20 mg/kg. (2.1)
- Administer Gleolan to patient orally 3 hours (range 2 to 4 hours) before anesthesia. (2.1)
- See Full Prescribing Information for reconstitution information. (2.2)
- Use appropriate visualization techniques with appropriate surgical microscopes and light source filters. (2.4)

3 DOSAGE FORMS AND STRENGTHS

For oral solution: 1,500 mg aminolevulinic acid hydrochloride lyophilized powder, equivalent to 1,170 mg aminolevulinic acid per vial. The reconstituted aminolevulinic acid hydrochloride solution contains 30 mg per mL and is clear and colorless to slightly yellowish in color. (3)

4 CONTRAINDICATIONS

- Hypersensitivity to aminolevulinic acid (ALA) or porphyrins. (4, 5.3, 6.2)
- Acute or chronic types of porphyria. (4)

5 WARNINGS AND PRECAUTIONS

- Phototoxic reactions: Do not administer phototoxic drugs (St. John's wort, griseofulvin, thiazide diuretics, sulfonylureas, phenothiazines, sulphonamides, quinolones and tetracyclines), and topical preparations containing ALA for 24 hours during the perioperative period. Reduce exposure to sunlight or room lights for 48 hours after oral administration of Gleolan. (5.1, 7)
- Risk of misinterpretation: Non-fluorescing tissue in the surgical field does not rule out the presence of tumor. (5.2, 14)

6 ADVERSE REACTIONS

- Adverse reactions occurring in >1% of patients in the week following surgery were pyrexia, hypotension, nausea, and vomiting. (6.1)
- Adverse reactions occurring in < 1% of patients in the first 6 weeks after surgery were: chills, photosensitivity reaction, solar dermatitis, hypotension, abnormal liver function test, and diarrhea. (6.1)
- Neurologic events related to the surgical procedure occurred in 29% of patients and included: aphasia, hemiparesis, hemianopia, headache, seizure, hemiplegia, monoparesis, hypoesthesia, and brain edema. (6.1)
- Elevated liver enzymes occurred in clinical studies. There were no cases of liver failure. (6.1)

To report SUSPECTED ADVERSE REACTIONS, contact NXDC toll-free at (844) 517-5252 and adverseevents@nxdevcorp.com or FDA at 1-800-FDA-1088 or www.fda.gov/medwatch.

FULL PRESCRIBING INFORMATION

1 INDICATIONS AND USAGE

Gleolan is indicated in patients with glioma [suspected World Health Organization (WHO) Grades III or IV on preoperative imaging] as an adjunct for the visualization of malignant tissue during surgery.

2 DOSAGE AND ADMINISTRATION

2.1 Recommended Dose

- For oral use only
- The recommended oral dose of reconstituted Gleolan is 20 mg / kg body weight. More than 1 vial may be required.

2.2 Reconstitution of Gleolan

Gleolan powder must be reconstituted prior to administration by a healthcare provider according to the following instructions:

- Determine the total number of vials needed to achieve the intended dose for the patient according to the equation below (rounded up to the nearest whole vial):
  # of vials = | Patient Body Weight (kg)
  # of vials = | 75 kg / vial
- Completely remove the white cap and aluminum crimp seal from each vial.
- Remove and retain the rubber stopper from the vial.
- Using an appropriate volumetric measuring device (e.g., flask, graduated cylinder, dosing syringe), measure 50 mL of drinking water and add to each vial containing 1,500 mg of Gleolan.
- Gently swirl the vial to completely dissolve the powder.
- The resulting reconstituted solution (30 mg of Gleolan per mL) is clear and colorless to slightly yellowish.
- If required, replace the stopper and store reconstituted solution for up to 24 hours at room temperature prior to administration.

2.3 Gleolan Administration

Gleolan is for ORAL USE ONLY. The reconstituted Gleolan solution is administered according to the following steps:

- Calculate the administration volume, in mL, to achieve the intended dose according to the following equation:
  Administration Volume (mL) = | Patient Body Weight (kg) * 20 mg/kg
  Administration Volume (mL) = | 30 mg/mL
- Transfer the entire contents of the prepared vial(s) into an appropriate dosing container (e.g., oral medicine bottle); ensure the entire contents of the vials are transferred.
- After transfer, discard the empty vial(s).
- Using a disposable volumetric syringe, remove the administration volume of reconstituted Gleolan solution from the dosing container and transfer to a separate oral dosing container.
- Discard unneeded volume of Gleolan solution.
- Administer orally 3 hours (range 2 to 4 hours) prior to induction of anesthesia.

2.4 Imaging Instructions

- Gleolan should be used with a standard surgical operating microscope adapted with a blue light emitting light source (power density 40-80 mW/cm^2) and ancillary excitation and emission filters to visualize fluorescence excitation in the wavelength of 375 to 440 nm and for observation from 620 to 710 nm. Filters transmit porphyrin fluorescence as red-violet, as well as a fraction of backscattered blue excitation light necessary for distinguishing nonfluorescing tissue.
- Gleolan should only be used by neurosurgeons who have completed a training program on use of fluorescence in surgery. Training is provided by the distributor.

3 DOSAGE FORMS AND STRENGTHS

For oral solution: 1,500 mg aminolevulinic acid hydrochloride (ALA HCl) lyophilized powder, equivalent to 1,170 mg aminolevulinic acid (ALA) , in a 50 mL single-dose clear, colorless, glass vial with rubber stopper. After reconstitution with 50 mL drinking water, the solution contains 30 mg per mL of aminolevulinic acid hydrochloride (equivalent to 23.4 mg per mL of aminolevulinic acid) and is clear and colorless to slightly yellowish in color.

4 CONTRAINDICATIONS

- Hypersensitivity to the aminolevulinic acid (ALA) or porphyrins. [see Warnings and Precautions (5.3)]
- Acute or chronic types of porphyria, due to potential ineffectiveness of the drug in these patients.

5 WARNINGS AND PRECAUTIONS

5.1 Risk of Phototoxic Reaction

Due to the risk of phototoxic reactions, do not administer phototoxic drugs (St. John's wort, griseofulvin, thiazide diuretics, sulfonylureas, phenothiazines, sulphonamides, quinolones and tetracyclines), and topical preparations containing ALA for 24 hours during the perioperative period [see Drug Interactions (7)]. Reduce exposure to sunlight or room lights for 48 hours after administration of Gleolan.

5.2 Risk of Misinterpretation

Errors may occur with the use of Gleolan for intraoperative visualization of malignant glioma, including false negatives and false positives. Non-fluorescing tissue in the surgical field does not rule out the presence of tumor in patients with glioma [see Clinical Studies (14)]. Fluorescence may be seen in areas of inflammation or metastases from other tumor types.

5.3 Hypersensitivity Reactions

Hypersensitivity reactions, including serious hypersensitivity reactions have occurred; these reactions include anaphylactic shock, swelling, and urticaria [see Contraindications (4), Adverse Reactions (6.2)]. Always have cardiopulmonary resuscitation personnel and equipment readily available and monitor all patients for hypersensitivity reactions.

6 ADVERSE REACTIONS

6.1 Clinical Trial Experience

Because clinical trials are conducted under widely varying conditions, adverse reaction rates observed in the clinical trials of a drug cannot be directly compared to rates in the clinical trials of another drug and may not reflect the rates observed in practice.

The safety of Gleolan is supported by data from 5 open label clinical studies, which included 527 patients with glioma who received ALA HCl. Adverse reactions that occurred in > 1% of patients in the week following surgery were pyrexia, hypotension, nausea, and vomiting. Adverse reactions occurring in the first 6 weeks after surgery in < 1% of patients were: chills, photosensitivity reaction, solar dermatitis, hypotension, abnormal liver function test, and diarrhea. One patient experienced respiratory failure due to drug overdose [see Overdosage (10)].

Neurologic Events

Nervous system disorders occurred in 29% of patients within the first week after surgery. Events occurring in > 1% of patients included aphasia (8%), hemiparesis (7.8%), hemianopsia (3.2%), headache (2.7%), seizure (1.9%), hemiplegia (1.9%), monoparesis (1.3%) and hypoesthesia (1.1%). Brain edema occurred in < 1 % of patients in the first 6 weeks after surgery. In a randomized clinical trial (Study 3), the numbers of serious neurologic adverse events in the post operative period were higher in patients randomized to ALA fluorescence arm compared to the control arm. An imbalance was notable for the adverse events aphasia, ataxia, convulsion and hemianopsia, and is likely related to the higher amount of brain resection performed in the ALA arm. At longer follow up periods, the numbers between the two arms appeared similar [see Clinical Trials (14)].

Elevated Liver Enzymes

Worsening of ≥ 2 Common Toxicity Criteria (CTC) grades in alanine aminotransferase (ALT) and gamma-glutamyl transferase (GGT) occurred in (15.8% and 11.6%, respectively) within the first week after surgery. Absolute levels ranged from 2 times to greater than 10 times the upper limit of normal (ULN) for each parameter. At 6 weeks, ALT remained elevated in 2.9% of patients (range 2 to greater than 5 X ULN), and GGT was elevated in 7.5% of patients (range 2 to greater than 10 X ULN). No cases of liver failure occurred.

6.2 Post Marketing Experience

The following adverse reactions are among those that have been identified during post-approval use of Gleolan outside of the United States. Because these reactions are reported voluntarily from a population of uncertain size, it is not always possible to reliably estimate their frequency or establish a causal relationship to drug exposure.

Immune Disorders: anaphylactic shock, angioedema, drug eruption, urticaria, erythema.

Metabolism and Nutrition Disorders: metabolic acidosis.

7 DRUG INTERACTIONS

Phototoxic Drugs

Patients exposed to a photosensitizing agent may experience a phototoxic skin reaction (severe sunburn). Due to the risk of possible phototoxic reactions, avoid administering phototoxic drugs such as St. John's wort, griseofulvin, thiazide diuretics, sulfonylureas, phenothiazines, sulphonamides, quinolones and tetracyclines, and topical preparations containing ALA for 24 hours before and after administration of Gleolan.

8 USE IN SPECIFIC POPULATIONS

8.1 Pregnancy

Risk Summary

There are no available human data on Gleolan in pregnant women to inform a drug associated risk of adverse developmental outcomes. In animal reproduction studies, no adverse developmental effects were observed with oral ALA HCl administration to pregnant rabbits during organogenesis at doses 3 times the maximum recommended human oral dose (see Data).

The estimated background risk of major birth defects and miscarriage for the indicated populations are unknown. All pregnancies have a background risk of birth defect, loss, or other adverse outcomes. In the U.S. general population, the estimated background risk of major birth defects and miscarriage in clinically recognized pregnancies is 2-4% and 15-20%, respectively.

Animal data

ALA HCl was administered to rabbits at oral doses of 15, 50 and 150 mg/kg/day [approximately 0.1, 0.6, and 3 times the maximum human recommended dose (MHRD), respectively based on AUC comparisons] from gestation days 6-18. The no-observed-adverse-effect level (NOAEL) for maternal toxicity was 50 mg/kg/day and the NOAEL for embryo-fetal developmental toxicity was 150 mg/kg/day.

8.2 Lactation

Risk summary

There are no data on the presence of ALA HCl in either human or animal milk, the effects on the breastfed infant, or the effects on milk production. The developmental and health benefits of breastfeeding should be considered along with the mother's clinical need for Gleolan and any potential adverse effects on the breastfed infant from Gleolan or from the underlying maternal condition.

Clinical Considerations

To decrease exposure to Gleolan to the breastfed infant, advise a lactating woman to pump and discard breast milk after the administration of Gleolan for 24 hours (i.e., 5 to 6 half-lives).

8.4 Pediatric Use

The safety and effectiveness of Gleolan in pediatric patients have not been established.

8.5 Geriatric Use

Of 527 subjects in clinical studies of Gleolan, 182 were 65 to < 75 years of age and 7 were ≥ 75 years of age. No overall differences in safety or effectiveness were observed between these subjects and younger subjects, and other reported clinical experience has not identified differences in responses between the elderly and younger patients, but greater sensitivity of some older individuals cannot be ruled out. No dose adjustment is required in elderly patients.

8.6 Patients with Renal Impairment

Because approximately one third of the ALA dose is excreted in urine as parent drug, ALA clearance may be reduced in patients with renal impairment; it is not known if dose adjustment is needed [see Clinical Pharmacology (12.3)].

8.7 Patients with Hepatic Impairment

The contribution of the liver to the elimination of ALA following Gleolan dosing is unknown. ALA clearance may be reduced in patients with hepatic impairment; it is not known if dose adjustment is needed [see Clinical Pharmacology (12.3)].

10 OVERDOSAGE

Overdosage has been associated with respiratory insufficiency and erythema. In the event of overdose, supportive measures should be provided as necessary, including protection from strong light sources.

11 DESCRIPTION

11.1 Chemical Properties

Gleolan (aminolevulinic acid hydrochloride) is an optical imaging agent for oral solution. The 50-mL, clear vial contains 1,500 mg of lyophilized aminolevulinic acid hydrochloride powder (equivalent to 1,170 mg aminolevulinic acid). After reconstitution, the product has a concentration of 30 mg aminolevulinic acid hydrochloride per mL (equivalent to 23.4 mg aminolevulinic acid per mL). The chemical name is 5-amino-4-oxo-pentanoic acid hydrochloride. The chemical formula for aminolevulinic acid hydrochloride is C5H10ClNO3. Its molecular weight is 167.59 g/mol with the following structural formula:

12 CLINICAL PHARMACOLOGY

12.1 Mechanism of Action

ALA occurs endogenously as a metabolite that is formed in the mitochondria from succinyl-CoA and glycine. Exogenous administration of ALA leads to accumulation of the ALA metabolite PpIX in tumor cells. The reason for the accumulation of PpIX in neoplastic brain tissue is not known.

During glioma surgery, Gleolan is used with an operating microscope adapted with a blue emitting light source (power density 40-80 mW/cm^2) and filters for excitation light of wavelength 375 to 440 nm, and observation at wavelengths of 620 to 710 nm. This allows tumor tissue to be visualized as red fluorescence. Tissue lacking sufficient PpIX concentrations appears blue.

12.2 Pharmacodynamics

The effect of the timing of the Gleolan dosing on fluorescence intensity in brain tissue is unknown. The relationship between systemic ALA plasma concentrations at the time of visualization and fluorescence intensity in brain is also unknown. The dose of 20 mg / kg provided stronger ALA-induced fluorescence in glioma tissue by both visual and spectrophotometric assessment compared to lower doses tested.

Cardiac Electrophysiology

Administration of the approved recommended dose of Gleolan did not prolong the QT interval to any clinically relevant extent.

12.3 Pharmacokinetics

In 12 healthy subjects, the mean half-life of ALA following the recommended dose of Gleolan solution was 0.9 ± 1.2 hours (mean ± std dev) with a range of 0.8 to 1.3 hours. Maximum concentrations of the PpIX metabolite (Tmax for PpIX) occurred with a median of 4 hours and a range of 1.2 to 7.8 hours. The elimination half-life of PpIX was 3.6 ± 1.8 hours (mean ± std dev) with a range of 1.2 to 7.8 hours.

Absorption

In 12 healthy subjects, the absolute bioavailability of ALA following the recommended dose of Gleolan solution was 100.0% ± 1.1 with a range of 78.5% to 131.2%. Maximum ALA plasma concentrations were reached with a median of 0.8 hour (range 0.5 – 1.0 hour).

Distribution

In in vitro experiments using ALA concentrations up to approximately 25% of the maximal concentration that occurs in plasma following the recommended dose of Gleolan solution, the mean protein binding of ALA was 12%.

Elimination

Metabolism

Exogenous ALA is metabolized to PpIX, but the fraction of administered ALA that is metabolized to PpIX is unknown. The average plasma AUC of PpIX is less than 6% of that of ALA.

Excretion

In 12 healthy subjects, excretion of parent ALA in urine in the 12 hours following administration of the recommended dose of Gleolan solution was 34 ± 8% (mean ± std dev) with a range of 27% to 57%.

Specific Populations

The effect of renal or hepatic impairment on the pharmacokinetics of ALA following Gleolan administration is unknown.

Drug Interaction Studies

In vitro studies suggest that phenytoin and other anti-convulsants may decrease cellular PpIX accumulation following Gleolan dosing.

ALA is not an inhibitor of CYP1A2, 2B6, 2C8, 2C9, 2C19, 2D6, or 3A.

13 NONCLINICAL TOXICOLOGY

13.1 Carcinogenesis, Mutagenesis, Impairment of Fertility

Carcinogenesis

No carcinogenicity studies have been conducted with Gleolan.

Mutagenesis

ALA HCl was not mutagenic in the Ames assay, HPRT-V79 mammalian cell mutagenicity test, the peripheral human lymphocyte chromosomal aberration assay and the in vivo mouse micronucleus test when studies were performed in the dark or under subdued lighting.

Impairment of Fertility

No fertility studies have been conducted with Gleolan.

14 CLINICAL STUDIES

The efficacy of 20 mg / kg ALA HCl was evaluated in 3 clinical studies (Study 1-3) involving patients, ages 18 to 75 years old, who had a preoperative MRI compatible with high-grade glioma (WHO Grade III or IV) and were undergoing surgical resection.

Study 1 was an open-label study of 33 patients with newly diagnosed high-grade glioma and Study 2 was an open-label study of 36 patients with recurrent high-grade glioma. In Studies 1 and 2, after initial debulking was carried out under white light, biopsies were obtained under fluorescent light from fluorescent and nonfluorescent sites. Presence of fluorescence (positive/negative) was compared to tumor status (true/false) using histopathology as the reference standard. True positives and false positives among fluorescent biopsies and true negatives and false negatives among nonfluorescent biopsies are provided in Table 1.

Study 3 was a randomized, multicenter study in 415 patients with a preoperative diagnosis of high-grade glioma by MRI. Patients were randomized in 1:1 ratio to ALA fluorescence arm or to white light control arm. Biopsies were obtained from tumor-core, tumor-margin and regions just distant to the tumor margins. In 349 patients high grade glioma was confirmed by a blinded central read and histopathology. The remaining patients were diagnosed with metastatic disease, abscess, low-grade glioma or other conditions.

In patients with confirmed high-grade glioma randomized to the ALA fluorescence arm, presence of fluorescence at a biopsy level was compared to tumor status using histopathology as the reference standard (Table 1). In 4 patients with low-grade glioma (WHO Grade I or II) who received ALA HCl, 9 out of 10 biopsies were false negative.

The extent of resection among patients with confirmed high-grade glioma in the ALA fluorescence arm was compared to that among patient in the control arm, with the "completeness" of resection being determined by a central blinded read of early post-surgical MRI. Percentage of patients who had "completeness" of resection was 64% in the ALA arm and 38% in the control arm, with the difference of 26% [95% CI: (16%, 36%)].

Table 1. Presence of Fluorescence Compared to Histopathology (biopsy level)
 | Study 1 (N=297) [N is Number of total (fluorescent and non-fluorescent) biopsies] | Study 2 (N=370) | Study 3 (N=479)
Number of Fluorescent Biopsies | 185 | 354 | 319
True Positive | 178 | 342 | 312
False Positive | 7 | 12 | 7
Number of Nonfluorescent Biopsies | 112 | 16 | 160
True Negative | 27 | 3 | 30
False Negative | 85 | 13 | 130

16 HOW SUPPLIED/STORAGE AND HANDLING

16.1 How Supplied

Gleolan (NDC 71469 -231- 01) is supplied as 1,500 mg of lyophilized aminolevulinic acid hydrochloride powder (equivalent to 1,170 mg aminolevulinic acid), for oral solution in a 50-mL clear, colorless, glass vial with a rubber stopper and an aluminum crimp seal.

16.2 Storage and Handling

Store at 25 °C (77 °F); excursions permitted to 15-30 °C (59-86 °F).

17 PATIENT COUNSELING INFORMATION

Advise patients that they may experience elevated liver enzymes (ALT and GGT) within the first week after surgery. This elevation may persist after 6 weeks.

Advise patients to reduce exposure to sunlight or room lights for 48 hours after administration of Gleolan due to risk of phototoxic reactions.

Manufactured for and Distributed by:
NX Development Corp.
870 Corporate Dr., Suite 403
Lexington, KY 40503

Product of Germany

APX1038/4

PRINCIPAL DISPLAY PANEL - 1,500 mg Vial Carton

NDC 71469-231-01
Rx only

Gleolan®
(aminolevulinic
acid hydrochloride)
for oral solution

1,500 mg

Reconstitute Prior To Use.

For Oral Use Only

SINGLE-DOSE VIAL.

Discard Unused Portion

One Vial

NX
Development Corp.